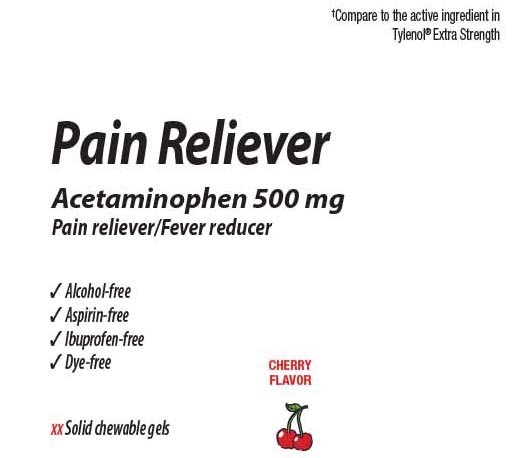 DRUG LABEL: Pain Reliever
NDC: 0363-9235 | Form: CHEWABLE GEL
Manufacturer: Walgreens
Category: otc | Type: HUMAN OTC DRUG LABEL
Date: 20260115

ACTIVE INGREDIENTS: ACETAMINOPHEN 500  mg/1 1
INACTIVE INGREDIENTS: ANHYDROUS CITRIC ACID; CORN SYRUP; SUCRALOSE; SUCROSE; MALIC ACID; WATER; SODIUM CITRATE

Drug Facts

Active ingredients (in each chewable gel)

Acetaminophen 500 mg

Purposes

Pain reliever/fever reducer

Uses

- temporarily relieves minor aches and pains due
  - headache
  - backache
  - toothache
  - the common cold
  - minor pain of arthritis
  - muscle aches
  - premenstrual and menstrual cramp
- temporarily reduces fever

Warnings

Liver warning: This product contains acetaminophen. Severe liver damage may occur if you take:

- more than 4,000 mg of acetaminophen in 24 hours
- with other drugs containing acetaminophen
- 3 or more alcoholic drinks every day while using this product

Allergy alert: Acetaminophen may cause severe skin reactions. Symptoms may include:

- skin reddening
- blisters
- rash

If a skin reaction occurs, stop use and seek medical help right away.

Do not use

- with any other drug containing acetaminophen (prescription or nonprescription). If you are not sure whether a drug contains acetaminophen, ask a doctor or pharmacist.
- if you are allergic to acetaminophen or any of the inactive ingredients in the product this product or any of its ingredients

Ask a doctor before use if you have

- liver disease
- a sodium-restricted diet

Ask a doctor or pharmacist before use if you are

taking blood thinning drug warfarin.

Stop use and ask a doctor if

- pain gets worse or lasts more than 10 days
- fever gets worse or lasts more than 3 days
- new symptoms occur
- redness or swelling is present

These could be signs of a serious condition.

If pregnant or breast-feeding,

ask a health professional before use.

Keep out of reach of children.

Overdose warning: In case of overdose, get medical help or contact a Poison Control Center (1-800-222-1222) right away: Quick medical attention is critical for adults as well as for children even if you do not notice any signs or symptoms.

Directions

- do not take more than directed (see overdose warning)
- adults and children 12 years and over:

- chew 2 gels every 6 hours while symptoms last
- do not take more than 12 gummies in 24 hours
- do not take for more than 10 days unless directed by a doctor

- children under 12 years: do not use

Other information

- each chewable gel contains: sodium 25 mg
- store at controlled room temperature 15-30ºC (59-86ºF)

Inactive ingredients

black carrot powder (for color), capol, citric acid anhydrous, corn syrup, malic acid, natural and artificial type flavors, purified water, sodium citrate, sucralose, sucrose

Questions or comments?

Call

Principal display panel

Compare to the active ingredient in Tylenol®

Pain Reliever/Fever reducer

Acetaminophen, 500 mg

Pain reliever/Fever reducer

- Alcohol-free
- Aspirin-free
- Ibuprofen-free
- Dye-free

†This product is not manufactured or distributed by McNeil Consumer Healthcare, distributor of Tylenol®

TAMPER EVIDENT: DO NOT USE IF PRINTED SAFETY SEAL UNDER CAP IS BROKEN OR MISSING.

Distributed by:

Product Label

WALGREENS Pain Reliever